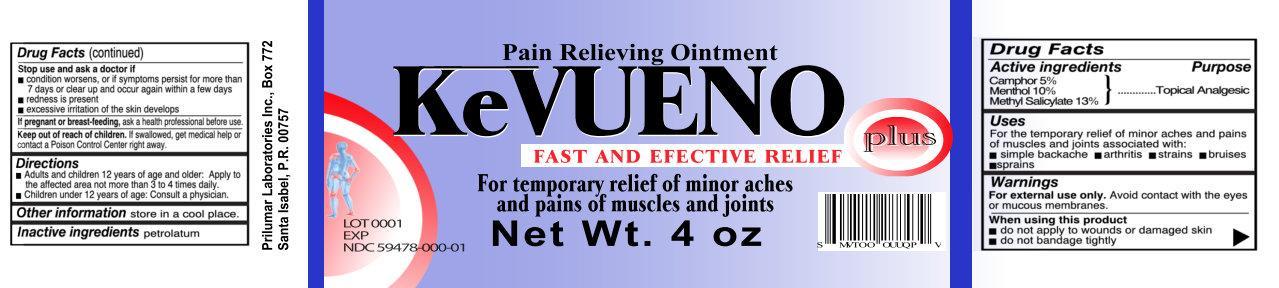 DRUG LABEL: KeVUENO Pain Relieving
NDC: 59478-000 | Form: OINTMENT
Manufacturer: Prilumar Laboratorios
Category: otc | Type: HUMAN OTC DRUG LABEL
Date: 20140115

ACTIVE INGREDIENTS: CAMPHOR (NATURAL) 5 g/100 g; MENTHOL 10 g/100 g; METHYL SALICYLATE 13 g/100 g
INACTIVE INGREDIENTS: PETROLATUM

KeVUENO Pain Relieving Ointment

Active Ingredients

Camphor 5%

Menthol 10%

Methyl Salicylate 13%

Purpose

Topical Analgesic

Uses

For the temporary relief of minor aches and pains of muscles and joints associated with:

- simple backache
- arthritis
- strains
- bruises
- sprains

Warnings

For external use only. Avoid contact with the eyes or mucous membranes.

When using this product

- do not apply to wounds or damaged skin
- do not bandage tightly

Stop use and ask a doctor if

- condition worsens, or if symptoms persist for more than 7 days or clear up and occur within a few days
- redness is present
- excessive irritation of the skin develops

If pregnant or breast-feeding, ask a health professional before use.

Keep out of reach of children. If swallowed, get medical help or contact a Poison Control Center right away.

Directions

- Adults and children 12 years of age and older: Apply to the affected area not more than 3 to 4 times daily
- Children under 12 years of age: Consult a physician.

Other information

store in a cool place.

Inactive Ingredients

petrolatum